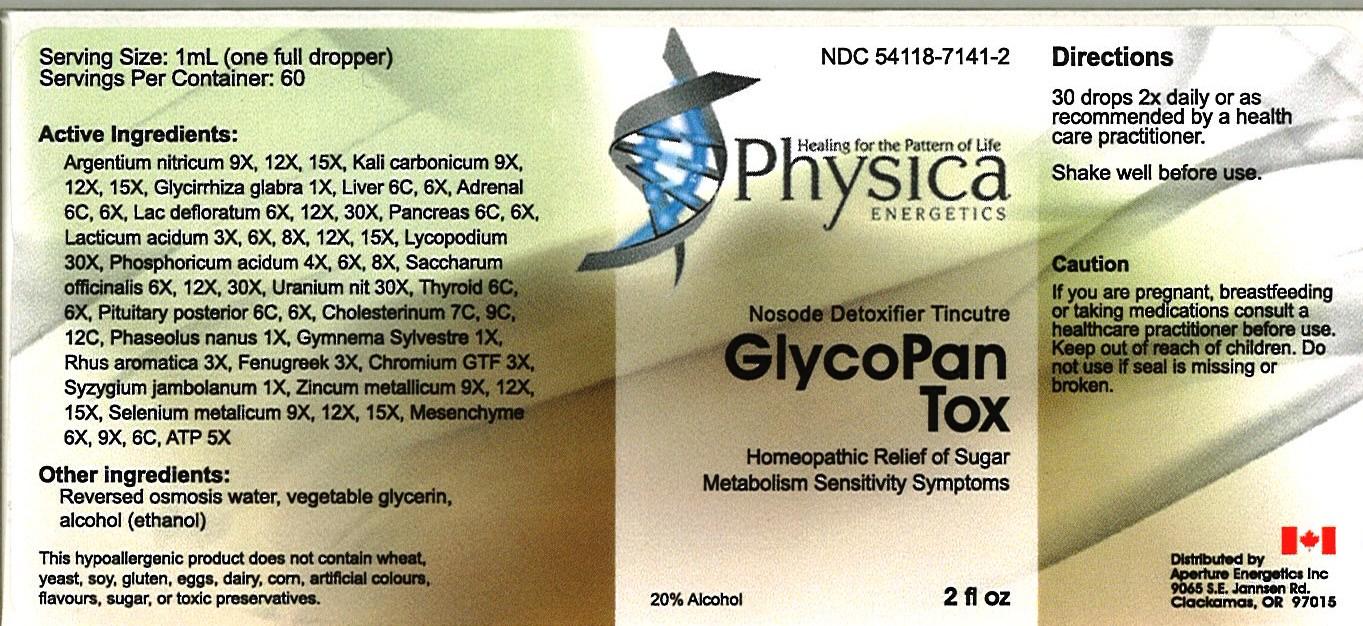 DRUG LABEL: GlycoPan Tox
NDC: 54118-7141 | Form: SOLUTION/ DROPS
Manufacturer: ABCO Laboratories, Inc.
Category: homeopathic | Type: HUMAN OTC DRUG LABEL
Date: 20130201

ACTIVE INGREDIENTS: SILVER NITRATE 9 [hp_X]/60 mL; POTASSIUM CARBONATE     9 [hp_X]/60 mL; GLYCYRRHIZA GLABRA 1 [hp_X]/60 mL; MAMMAL LIVER 6 [hp_C]/60 mL; BOS TAURUS ADRENAL GLAND 6 [hp_C]/60 mL; SKIM MILK 6 [hp_X]/60 mL; SUS SCROFA PANCREAS 6 [hp_C]/60 mL; LACTIC ACID, DL- 3 [hp_X]/60 mL; LYCOPODIUM CLAVATUM SPORE 30 [hp_X]/60 mL; PHOSPHORIC ACID 4 [hp_X]/60 mL; SUCROSE 6 [hp_X]/60 mL; URANYL NITRATE HEXAHYDRATE 30 [hp_X]/60 mL; THYROID, UNSPECIFIED 6 [hp_C]/60 mL; BOS TAURUS PITUITARY GLAND 6 [hp_C]/60 mL; CHOLESTEROL 7 [hp_C]/60 mL; KIDNEY BEAN 1 [hp_X]/60 mL; GYMNEMA SYLVESTRE LEAF 1 [hp_X]/60 mL; RHUS AROMATICA ROOT BARK 3 [hp_X]/60 mL; FENUGREEK SEED 3 [hp_X]/60 mL; CHROMIUM 3 [hp_X]/60 mL; SYZYGIUM CUMINI SEED 1 [hp_X]/60 mL; ZINC 9 [hp_X]/60 mL; SELENIUM 9 [hp_X]/60 mL; BOS TAURUS MESENCHYME 6 [hp_X]/60 mL; ADENOSINE TRIPHOSPHATE 5 [hp_X]/60 mL
INACTIVE INGREDIENTS: WATER; GLYCERIN; ALCOHOL

GlycoPan Tox

Active Ingredients:

Argentium nitricum 9x, 12x, 15x

Kali carbonicum 9x, 12x, 15x

Glycirrhiza glabra 1x

Liver 6c, 6x

Adrenal 6c, 6x

Lac defloratum 6x, 12x, 30x

Pancreas 6c, 6x

Lacticum acidum 3x, 6x, 8x, 12x, 15x

Lycopodium 30x

Phosphoricum acidum 4x, 6x, 8x

Saccharum officinalis 6x, 12x, 30x

Uranium nit 30x

Thyroid 6c, 6x

Pituitary posterior 6c, 6x

Cholesterinum 7c, 9c, 12c

Phaseolus nanus 1x

Gymnema Sylvestre 1x

Rhus aromatica 3x

Fenugreek 3x

Chromium GTF 3x

Syzygium jambolanum 1x

Zincum metallicum 9x, 12x, 15x

Selenium metalicum 9x, 12x, 15x

Mesenchyme 6x, 9x, 6c

ATP 5x

PURPOSE

- Homeopathic Relief of Sugar Metabolism Sensitivity Symptoms

Keep out of reach of children

INDICATIONS AND USAGE

- 30 drops 2X daily
- or as recommended by a health care practitioner
- Shake well before use

WARNINGS

- If you are pregnant, breastfeeding or taking medications consult a health care practitioner before use.
- Keep out of reach of children
- Do not use if seal is missing or broken

DOSAGE AND ADMINISTRATION

30 drops 2X daily or as recommended by a health care practitioner
Shake well before use

INACTIVE INGREDIENT

- Reverse osmosis water
- Vegetabe glycerin
- Alcohol (ethanol)